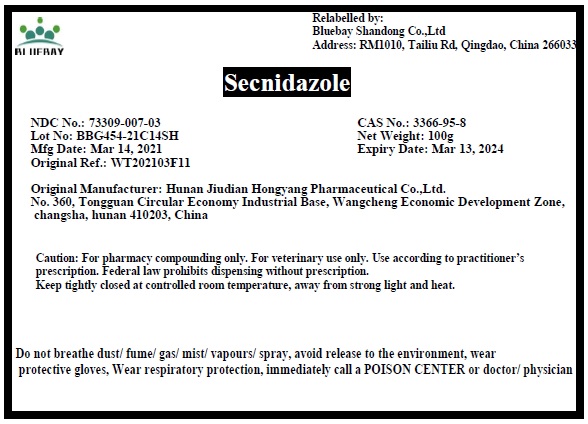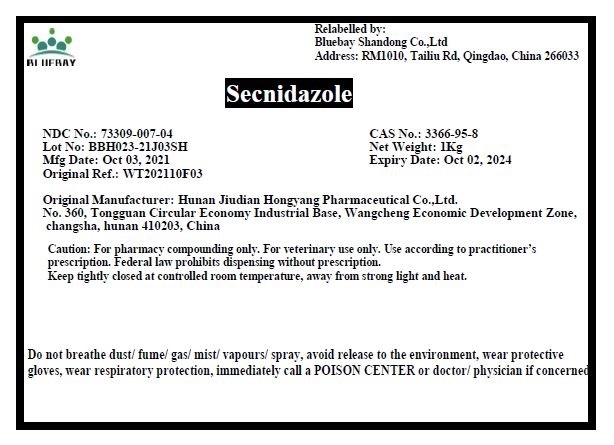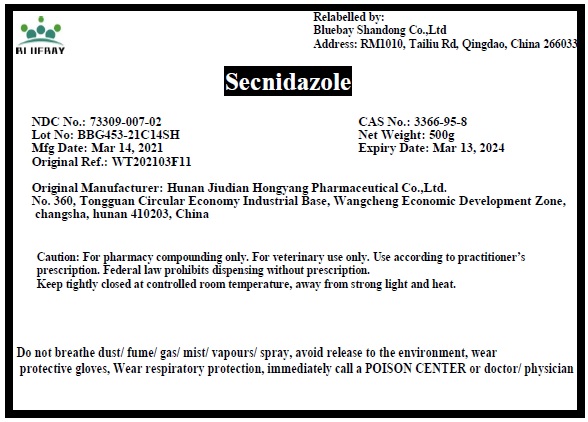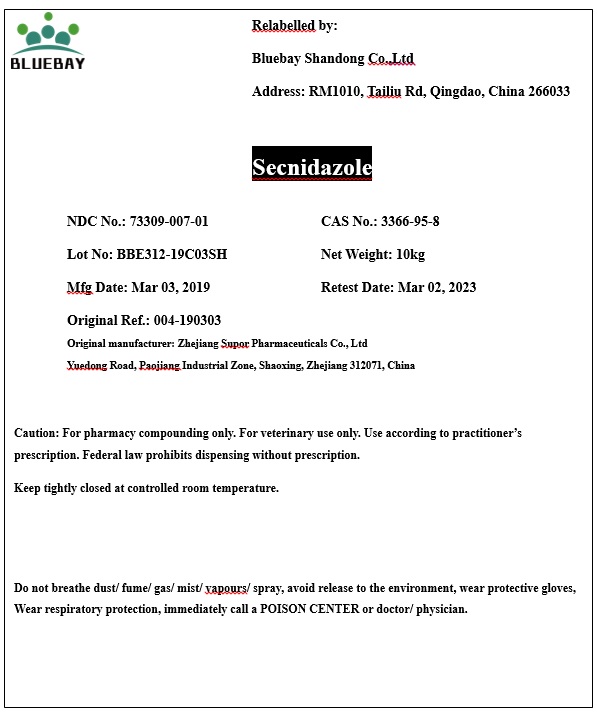 DRUG LABEL: Secnidazole
NDC: 73309-007 | Form: POWDER
Manufacturer: BLUEBAY SHANDONG CO.,LTD
Category: other | Type: BULK INGREDIENT
Date: 20220112

ACTIVE INGREDIENTS: SECNIDAZOLE 1 kg/1 kg

Secnidazole